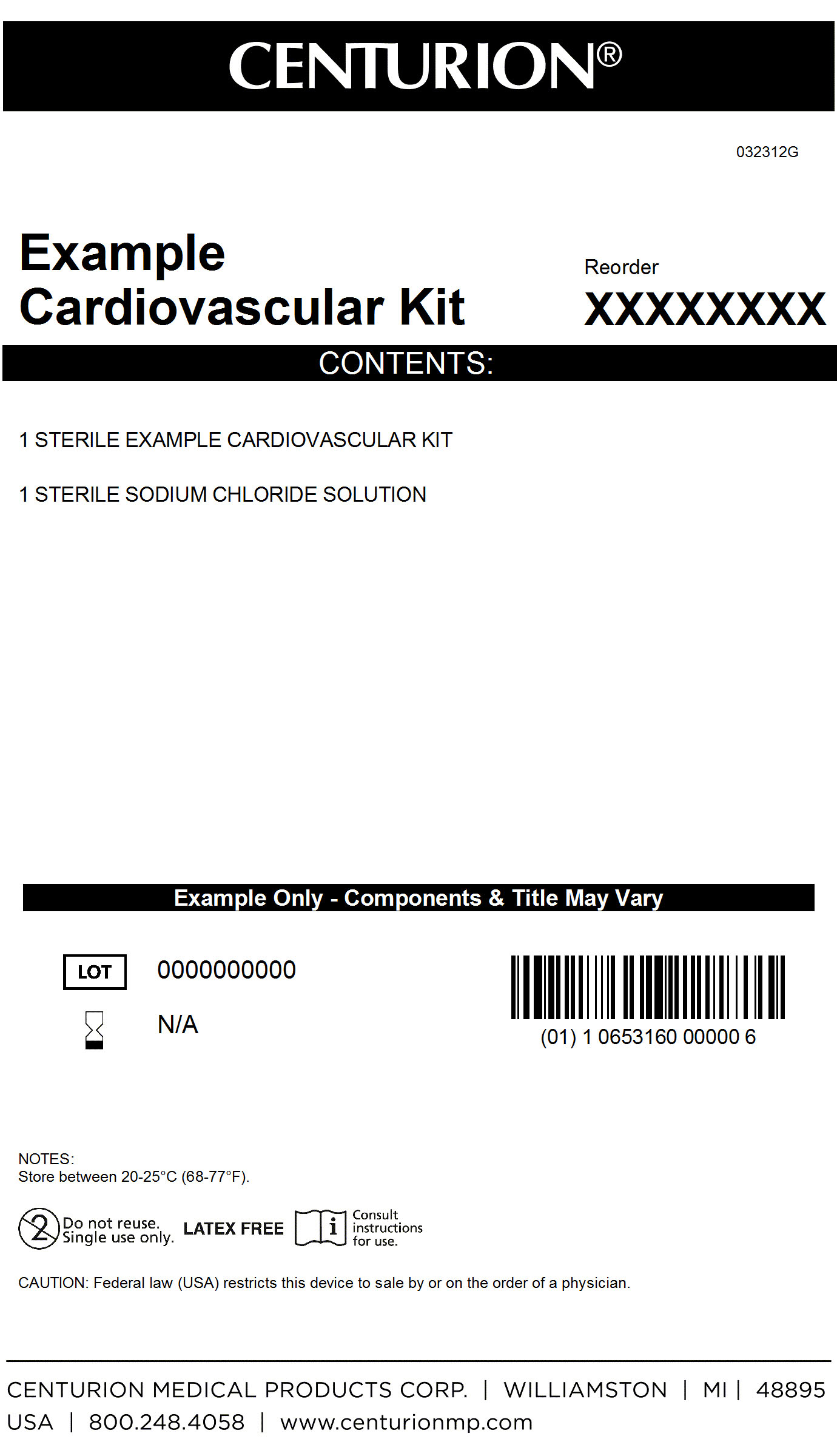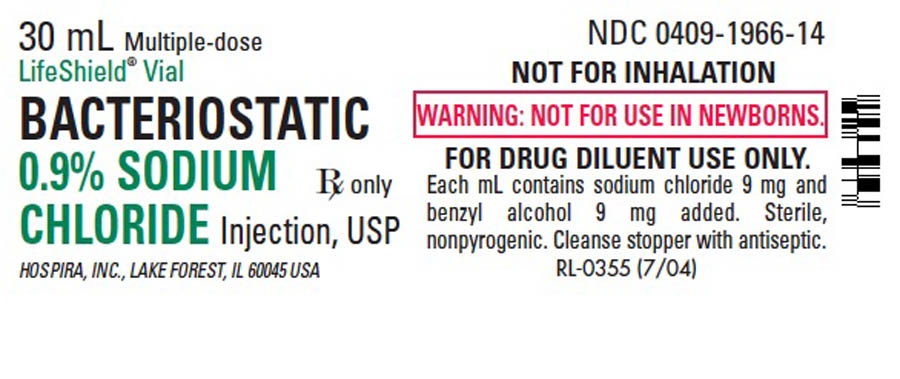 DRUG LABEL: Cardiovascular Kit
NDC: 24840-1130 | Form: KIT | Route: INTRAVENOUS
Manufacturer: Centurion Medical Products
Category: other | Type: MEDICAL DEVICE
Date: 20120523

ACTIVE INGREDIENTS: SODIUM CHLORIDE 9 mg/1 mL
INACTIVE INGREDIENTS: BENZYL ALCOHOL 9 mg/1 mL; WATER

Cardiovascular Kit

DESCRIPTION

This preparation is designed for parenteral use only after addition of drugs that require dilution or must be dissolved in an aqueous vehicle prio to injection. Bacteriostatic 0.9% sodium chloride injections, USP is a sterile, nonpyrogenic, isotonic solution of sodium chloride injection in water for injection. Each mililiter (mL) contains sodium chloride 9 mg and 0.9% benzyl alcohol added as a bacteriostatic preservative. May contain hydrochloric acid for pH adjustment. It is supplied in a multiple-dose container from which repeated withdrawls may be made to dilute or dissolve drugs for medication. The pH is 5.0 (4.5 to 7.0). Sodium Chloride, USP is chemically designated NaCl, a white, crystalline powder freely soluable in water. The semi-ridgid vial is fabricated from a specially formulated plyolefin. It is a copolymer of ethylene and propylene. The safety of the plastic has been confirmed by tests in animals according to USP biological standards for plastic containers. The container requires novapor barrier to maintain the proper drug concentration.

Cardiovascular Kit Primary Label

MM1

Sodium Chloride Label

MM1